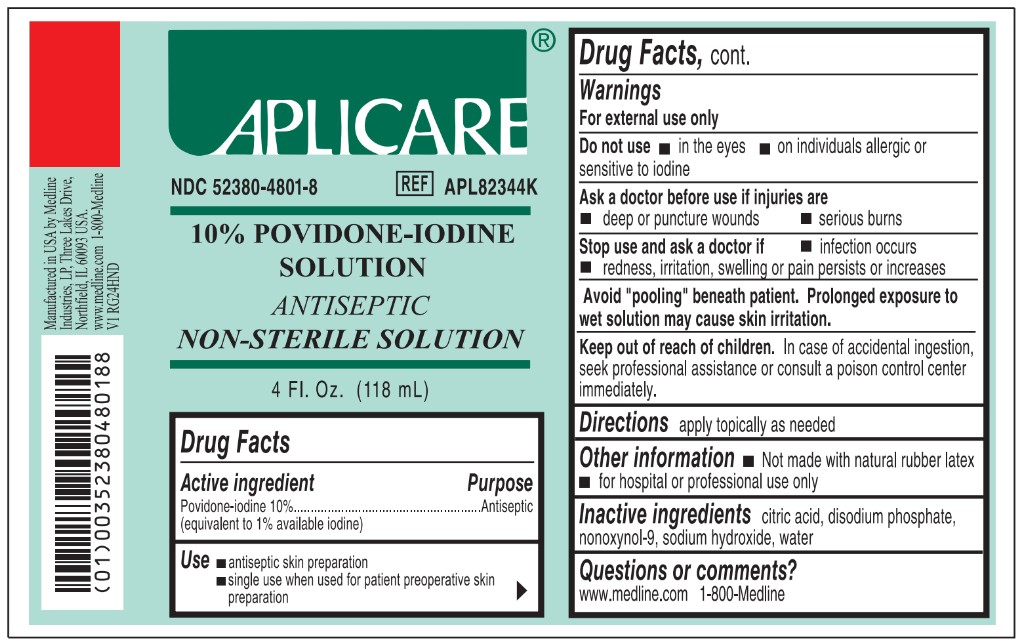 DRUG LABEL: Aplicare Povidone-Iodine
NDC: 52380-4801 | Form: SOLUTION
Manufacturer: Aplicare Products, LLC
Category: otc | Type: HUMAN OTC DRUG LABEL
Date: 20250902

ACTIVE INGREDIENTS: POVIDONE-IODINE 10 mg/1 mL
INACTIVE INGREDIENTS: CITRIC ACID MONOHYDRATE; SODIUM PHOSPHATE, DIBASIC; SODIUM HYDROXIDE; NONOXYNOL-9; WATER

4801 Aplicare Povidone-Iodine

Active ingredient

Povidone-iodine 10%

(equivalent to 1% available iodine)

Purpose

Antiseptic

Use

- • antiseptic skin preparation
- • single use when used for patient preoperative skin preparation

Warnings

- For external use only
- Avoid "pooling" beneath patient. Prolonged exposure to wet solution may cause skin irritation.

Do not use

- • in the eyes
- • on individuals allergic or sensitive to iodine

Ask a doctor before use if injuries are

- • deep puncture wounds
- • serious burns

Stop use and ask a doctor if

- • infection occurs
- • redness, irritation, swelling or pain persists or increases

Keep out of reach of children.

In case of accidental ingestion, seek professional assistance or consult a poison control center immediately.

Directions

apply topically as needed

Other information

- • not made with natural rubber latex
- • for hospital or professional use only

Inactive ingredients

citric acid, disodium phosphate, nonoxynol-9, sodium hydroxide, water

Questions or comments?

www.medline.com 1 800-Medline

Manufacturing Information

Manufactured in USA by Medline Industries, LP,

Three Lakes Drive, Northfield, IL 60093 USA.

www.medline.com 1-800-Medline

REF: APL82344K

V1 RG24HND